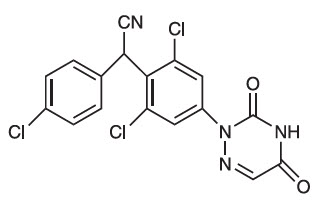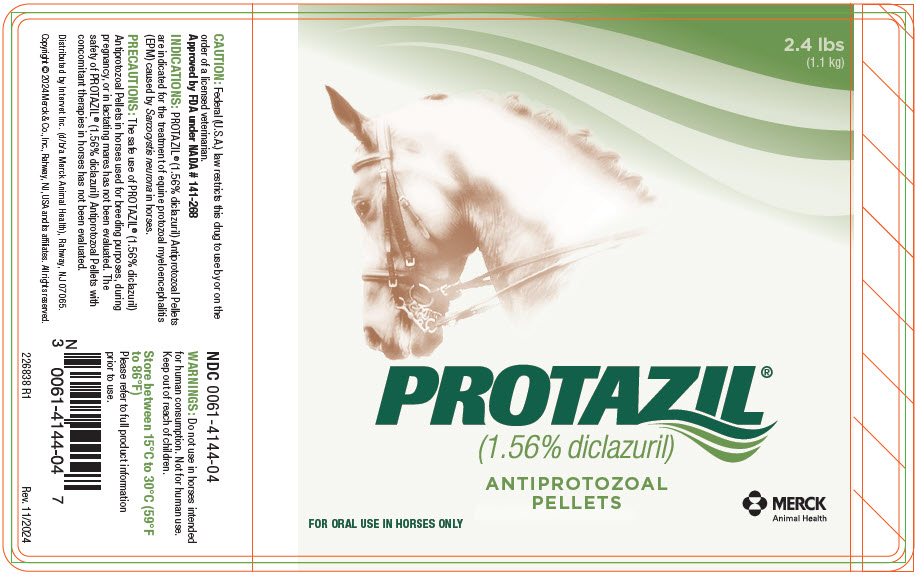 DRUG LABEL: Protazil
NDC: 0061-4144 | Form: PELLET
Manufacturer: Merck Sharp & Dohme Corp.
Category: animal | Type: PRESCRIPTION ANIMAL DRUG LABEL
Date: 20250430

ACTIVE INGREDIENTS: DICLAZURIL 16 g/1 kg

PROTAZIL®
(1.56% diclazuril)
ANTIPROTOZOAL PELLETS

FOR ORAL USE IN HORSES ONLY

CAUTION

Federal (U.S.A.) law restricts this drug to use by or on the order of a licensed veterinarian.

Approved by FDA under NADA # 141-268

DESCRIPTION

Diclazuril, (±)-2,6-dichloro-α-(4-chlorophenyl)-4-(4,5-dihydro-3,5-dioxo-1,2,4-triazin-2(3H)-yl)benzeneacetonitrile, has a molecular formula of C17H9CI3N4O2, a molecular weight of 407.64, and a molecular structure as follows:

Diclazuril is an anticoccidial (antiprotozoal) compound with activity against several genera of the phylum Apicomplexa. PROTAZIL® (diclazuril) is supplied as oral pellets containing 1.56% diclazuril to be mixed as a top-dress in feed. Inert ingredients include dehydrated alfalfa meal, wheat middlings, cane molasses and propionic acid (preservative).

INDICATIONS

PROTAZIL® (1.56% diclazuril) Antiprotozoal Pellets are indicated for the treatment of equine protozoal myeloencephalitis (EPM) caused by Sarcocystis neurona in horses.

DOSAGE AND ADMINISTRATION

Dosage: PROTAZIL® (1.56% diclazuril) is administered as a top dress in the horse's daily grain ration at a rate of 1 mg diclazuril per kg (0.45 mg diclazuril/lb) of body weight for 28 days. The quantity of PROTAZIL® necessary to deliver this dose is 64 mg pellets per kg (29 mg pellets/lb) of body weight.

Administration: To achieve this dose, weigh the horse (or use a weigh tape). Scoop up PROTAZIL® to the level (cup mark) corresponding to the dose for the horse's body weight using the following chart:

Weight Range of Horse (lb) | mLs of Pellets | Weight Range of Horse (lb) | mLs of Pellets
275 - 524 | 20 | 1275 - 1524 | 60
525 - 774 | 30 | 1525 - 1774 | 70
775 - 1024 | 40 | 1775 - 2074 | 80
1025 - 1274 | 50 | - | -

One 2.4-lb bucket of PROTAZIL® will treat one 1274-lb horse for 28 days.

CONTRAINDICATIONS

Use of PROTAZIL® (1.56% diclazuril) Antiprotozoal Pellets is contraindicated in horses with known hypersensitivity to diclazuril.

WARNINGS

For use in horses only. Do not use in horses intended for human consumption. Not for human use. Keep out of reach of children.

PRECAUTIONS

The safe use of PROTAZIL® (1.56% diclazuril) Antiprotozoal Pellets in horses used for breeding purposes, during pregnancy, or in lactating mares has not been evaluated. The safety of PROTAZIL® (1.56% diclazuril) Antiprotozoal Pellets with concomitant therapies in horses has not been evaluated.

ADVERSE REACTIONS

There were no adverse effects noted in the field study which could be ascribed to diclazuril.

CONTACT INFORMATION

For technical information or to report a suspected adverse event, please contact Merck Animal Health at 1-800-224-5318 or https://www.merck-animal-health-usa.com. Safety Data Sheets (SDSs) can be found at https://www.merck.com/products/safety-datasheets/#.

For additional information about reporting adverse drug experiences for animal drugs, contact FDA at 1-888-FDA-VETS or https://www.fda.gov/reportanimalae.

CLINICAL PHARMACOLOGY

The effectiveness of diclazuril in inhibiting merozoite production of Sarcocystis neurona and S. falcatula in bovine turbinate cell cultures was studied by Lindsay and Dubey (2000).^1 Diclazuril inhibited merozoite production by more than 80% in cultures of S. neurona or S. falcatula treated with 0.1 ng/mL diclazuril and greater than 95% inhibition of merozoite production (IC95) was observed when infected cultures were treated with 1.0 ng/mL diclazuril. The clinical relevance of the in vitro cell culture data has not been determined.

PHARMACOKINETICS IN THE HORSE

The oral bioavailability of diclazuril from the PROTAZIL® (1.56% diclazuril) Antiprotozoal Pellets at a 5 mg/kg dose rate is approximately 5%. Related diclazuril concentrations in the cerebrospinal fluid (CSF) range between 1% and 5% of the concentrations observed in the plasma. Nevertheless, based upon equine pilot study data, CSF concentrations are expected to substantially exceed the in vitro IC95 estimates for merozoite production (Dirikolu et al., 1999)^2. Due to its long terminal elimination half-life in horses (approximately 43-65 hours), diclazuril accumulation occurs with once-daily dosing. Corresponding steady state blood levels are achieved by approximately Day 10 of administration.

EFFECTIVENESS

Two hundred and fourteen mares, stallions, and geldings of various breeds, ranging in age from 9.6 months to 30 years, were enrolled in a multi-center field study. All horses were confirmed EPM-positive based on the results of clinical examinations and laboratory testing, including CSF Western Blot analyses. Horses were administered PROTAZIL® (1.56% diclazuril) Antiprotozoal Pellets at doses of 1, 5, or 10 mg diclazuril/kg body weight as a top-dress on their daily grain ration for 28 days. The horses were then evaluated for clinical changes via a modified Mayhew neurological scale on Day 48 as follows:

0. Normal, neurological deficits not detected.
1. Neurological deficits may be detectable at normal gaits; signs exacerbated with manipulative procedures (e.g., backing, turning in tight circles, walking with head elevation, truncal swaying, etc.).
2. Neurological deficit obvious at normal gaits or posture; signs exacerbated with manipulative procedures.
3. Neurological deficit very prominent at normal gaits: horses give the impression they may fall (but do not) and buckle or fall with manipulative procedures.
4. Neurological deficit is profound at normal gait: horse frequently stumbles or trips and may fall at normal gaits or when manipulative procedures were utilized.
5. Horse is recumbent, unable to rise.

Each horse's response to treatment was compared to its pre-treatment values. Successful response to treatment was defined as clinical improvement of at least one grade by Day 48 ± conversion of CSF to Western Blot-negative status for S. neurona or achievement of Western Blot-negative CSF status without improvement of 1 ataxia grade.

Forty-two horses were initially evaluated for effectiveness and 214 horses were evaluated for safety. Clinical condition was evaluated by the clinical investigator's subjective scoring and then corroborated by evaluation of the neurological examination videotapes by a masked panel of three equine veterinarians. Although 42 horses were evaluated for clinical effectiveness, corroboration of clinical effectiveness via videotape evaluation was not possible for one horse due to missing neurologic examination videotapes. Therefore, this horse was not included in the success rate calculation. Based on the numbers of horses that seroconverted to negative Western Blot status, and the numbers of horses classified as successes by the clinical investigators, 28 of 42 horses (67%) at 1 mg/kg were considered successes. With regard to independent expert masked videotape assessments, 10 of 24 horses (42%) at 1 mg/kg were considered successes. There was no clinical difference in effectiveness among the 1, 5, and 10 mg/kg treatment group results. Adverse events were reported for two of the 214 horses evaluated for safety. In the first case, a horse was enrolled showing severe neurologic signs. Within 24 hours of dosing, the horse was recumbent, biting, and exhibiting signs of dementia. The horse died, and no cause of death was determined. In the second case, the horse began walking stiffly approximately 13 days after the start of dosing. The referring veterinarian reported that the horse had been fed grass clippings and possibly had laminitis.

ANIMAL SAFETY

PROTAZIL® (1.56% diclazuril) Antiprotozoal Pellets were administered to 30 horses (15 males and 15 females, ranging from 5 to 9 months of age) in a target animal safety study. Five groups of 6 horses each (3 males and 3 females) received 0, 5 (5X), 15 (15X), 25 (25X) or 50 (50X) mg diclazuril/kg (2.27mg/lb) body weight/day for 42 consecutive days as a top-dress on the grain ration of the horse. The variables measured during the study included: clinical and physical observations, body weights, food and water consumption, hematology, serum chemistry, urinalysis, fecal analysis, necropsy, organ weights, gross and histopathologic examinations. The safety of diclazuril top-dress administered to horses at 1 mg/kg once daily cannot be determined based solely on this study because of the lack of an adequate control group (control horses tested positive for the test drug in plasma and CSF). However, possible findings associated with the drug were limited to elevations in BUN, creatinine, and SDH and less than anticipated weight gain. Definitive test article-related effects were decreased grain/top-dress consumption in horses in the 50 mg/kg group.

In a second target animal safety study, PROTAZIL® (1.56% diclazuril) Antiprotozoal Pellets were administered to 24 horses (12 males and 12 females, ranging from 2 to 8 years of age). Three groups of 4 horses/sex/group received 0, 1, or 5 mg diclazuril/kg body weight/day for 42 days as a topdress on the grain ration of the horse. The variables measured during the study included physical examinations, body weights, food and water consumption, hematology, and serum chemistry. There were no test article-related findings seen during the study.

STORAGE INFORMATION

Store between 15°C to 30°C (59°F to 86°F).

HOW SUPPLIED

PROTAZIL® (1.56% diclazuril) Antiprotozoal Pellets are supplied in 2.4-lb (1.1-kg) buckets.

REFERENCES

1. Lindsay, D. S., and Dubey, J. P. 2000. Determination of the activity of diclazuril against Sarcocystis neurona and Sarcocystis falcatula in cell cultures. J. Parasitology, 86(1):164–166.
2. Dirikolu, L., Lehner, F., Nattrass, C., Bentz, B. G., Woods, W. E., Carter, W. E., Karpiesiuk, W. G., Jacobs, J., Boyles, J., Harkins, J. D., Granstrom, D. E. and Tobin, T. 1999. Diclazuril in the horse: Its identification and detection and preliminary pharmacokinetics.J. Vet. Pharmacol. Therap. 22:374–379.

Distributed by Intervet Inc. (d/b/a Merck Animal Health), Rahway, NJ 07065.
Copyright © 2024 Merck & Co., Inc., Rahway, NJ, USA and its affiliates.
All rights reserved.

Rev. 11/2024
226839 R3

PRINCIPAL DISPLAY PANEL - 1.1 kg Pellet Container Label

2.4 lbs
(1.1 kg)

PROTAZIL®
(1.56% diclazuril)

ANTIPROTOZOAL
PELLETS

FOR ORAL USE IN HORSES ONLY

MERCK
Animal Health